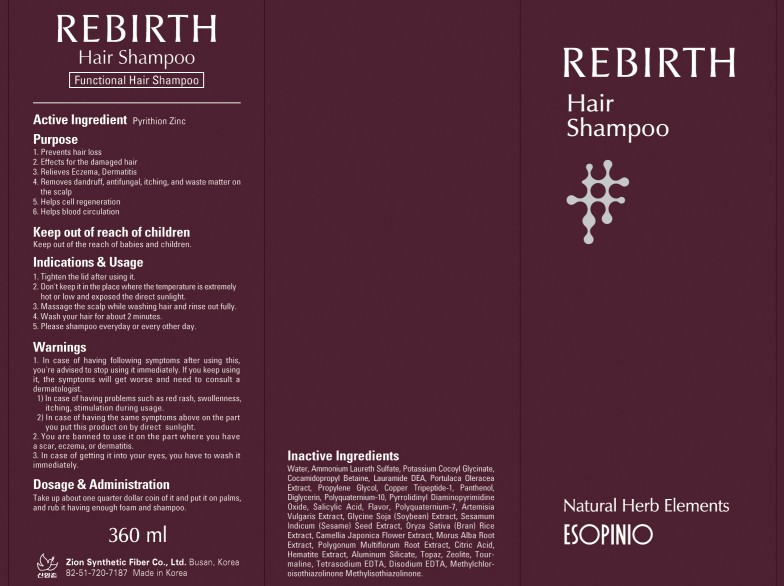 DRUG LABEL: REBIRTH HAIR
NDC: 44781-180 | Form: SHAMPOO
Manufacturer: ZION SYNTHETIC FIBER CO., LTD.
Category: otc | Type: HUMAN OTC DRUG LABEL
Date: 20110830

ACTIVE INGREDIENTS: PYRITHIONE ZINC 0.6 mL/360 mL
INACTIVE INGREDIENTS: Water; LAURIC DIETHANOLAMIDE; PURSLANE; Propylene Glycol; PANTHENOL; DIGLYCERIN; POLYQUATERNIUM-10 (400 CPS AT 2%); SALICYLIC ACID; POLYQUATERNIUM-7 (70/30 ACRYLAMIDE/DADMAC; 1600 KD); ARTEMISIA VULGARIS POLLEN; SESAME OIL; CAMELLIA JAPONICA FLOWER; MORUS ALBA ROOT; FALLOPIA MULTIFLORA ROOT; CITRIC ACID MONOHYDRATE; ALUMINUM SILICATE; EDETATE SODIUM; EDETATE DISODIUM

Drug Facts

Active ingredient: PYRITHIONE ZINC

Inactive ingredients:

Water, Ammonium Laureth Sulfate, Potassium Cocoyl Glycinate, Cocamidopropyl Betaine, Lauramide DEA, Portulaca Oleracea Extract, Propylene Glycol, Copper Tripeptide-1, Panthenol, Diglycerin, Polyquaternium-10, Pyrrolidinyl Diaminopy-rimidine Oxide, Salicylic Acid, Flavor, Polyquaternium-7, Artemisia Vulgaris Extract, Glycine Soja (Soybean) Extract, Sesamum Indicum (Sesame) Seed Extract,
Oryza Sativa (Bran) Rice Extract, Camellia Japonica Flower Extract, Morus Alba Root Extract, Polygonum Multiflorum Root Extract, Citric Acid, Hematite Extract, Aluminum Silicate, Topaz, Zeolite, Tourmaline, Tetrasodium EDTA, Disodium EDTA, Methylchloroisothiazolinone Methylisothiazolinone

Purpose:
Effects for the damaged hair
Removes dandruff, antifungal, itching, and waste matter on the scalp

Warnings:
In case of having following symptoms after using this, you're advised to stop using it immediately. If you keep using it, the symptoms will get worse and need to consult a dermatologist.
- In case of having problems such as red rash, swollenness, itching, stimulation during usage.
- In case of having the same symptoms above on the part you put this product on by direct sunlight.
You are banned to use it on the part where you have a scar, eczema, or dermatitis.
In case of getting it into your eyes, you have to wash it immediately.

Keep out of reach of children:
Keep out of the reach of babies and children.

Indication and usage:
Tighten the lid after using it.
Don't keep it in the place where the temperature is extremely hot or low and exposed the direct sunlight.
Massage the scalp while washing hair and rinse out fully.
Wash your hair for about 2 minutes.
Please shampoo everyday or every other day.

Dosage and administration:
Take up about one quarter dollar coin of it and put it on palms, and rub it having enough foam and shampoo.